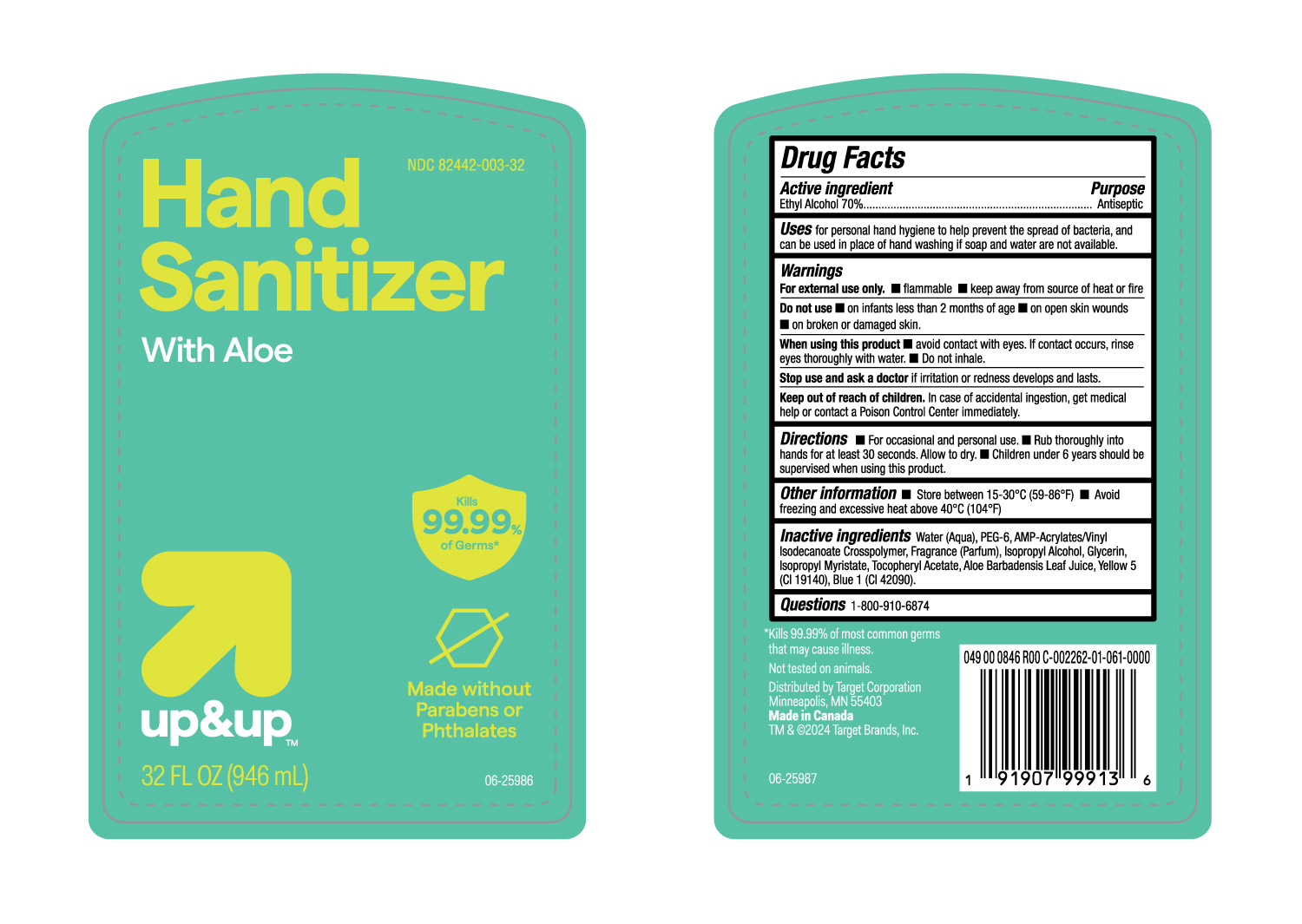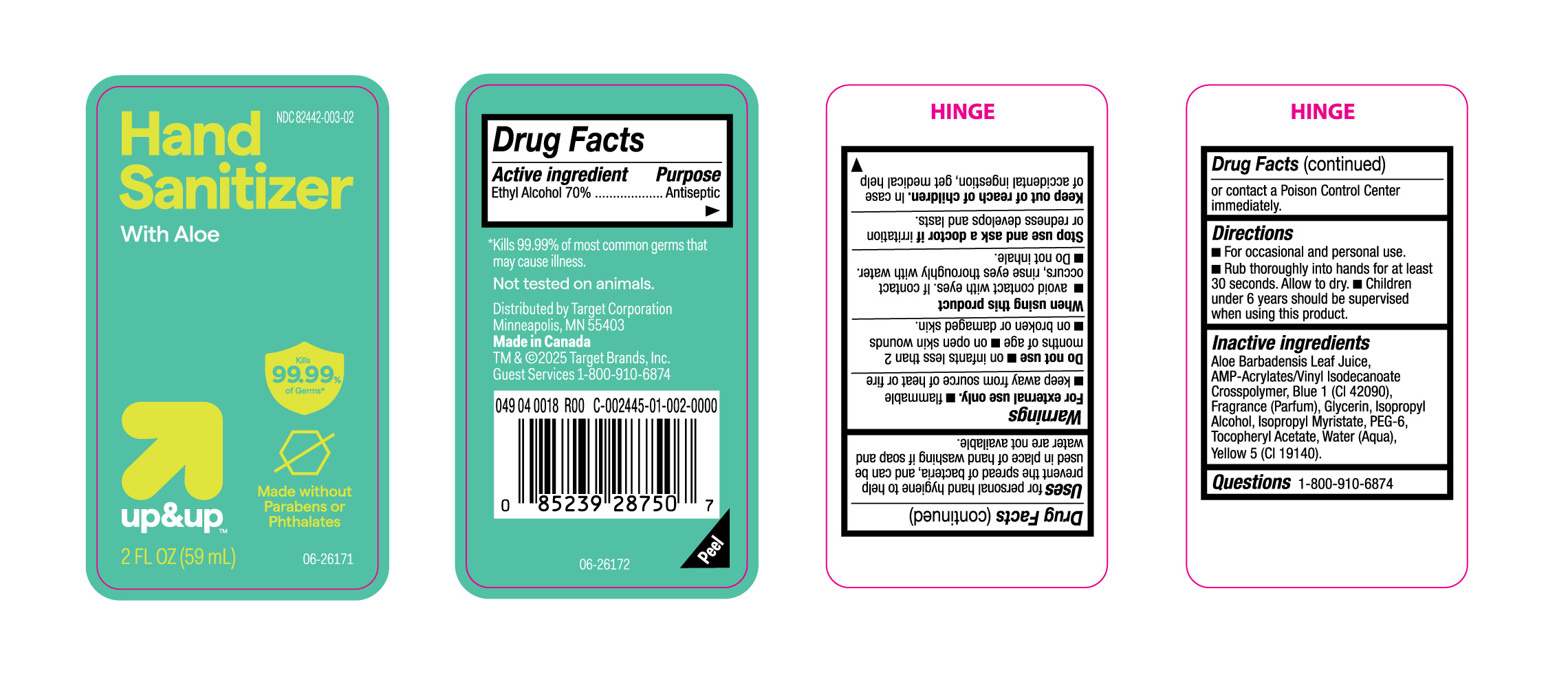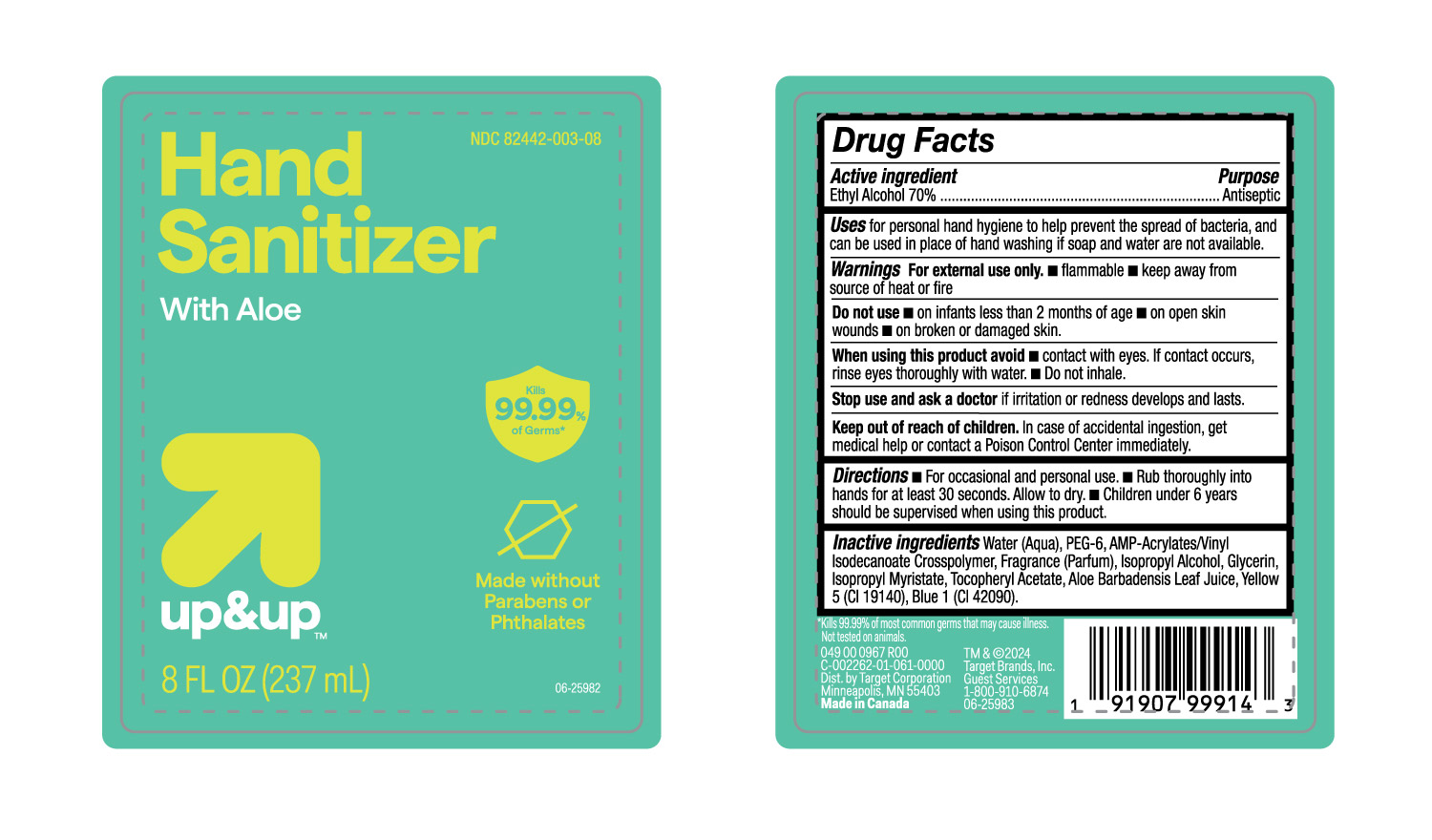 DRUG LABEL: Alcohol
NDC: 82442-003 | Form: GEL
Manufacturer: TARGET CORPORATION INC.
Category: otc | Type: HUMAN OTC DRUG LABEL
Date: 20240409

ACTIVE INGREDIENTS: ALCOHOL 70 mL/100 mL
INACTIVE INGREDIENTS: FRAGRANCE CLEAN ORC0600327; ISOPROPYL ALCOHOL; .ALPHA.-TOCOPHEROL ACETATE; ALOE VERA LEAF; FD&C YELLOW NO. 5; POLYETHYLENE GLYCOL 300; ACRYLATES/VINYL ISODECANOATE CROSSPOLYMER (10000 MPA.S NEUTRALIZED AT 0.5%); FD&C BLUE NO. 1; WATER; GLYCERIN; ISOPROPYL MYRISTATE

Hand Sanitizer with Aloe- Target- 82442-003

Active Ingredient

Ethyl Alcohol 70%

Purpose

Antiseptic

Uses

For personal hand hygine to help prevent the spread of bacteria, and can be used in place of hand washing if soap and water are not available.

Warnings

For external use only.

- Flammable
- Keep away from source of heat or fire.

Do not use

- On infants less than 2 months of age.
- On open skin wounds
- On broken or damaged skin

When using the product

- Avoid contact with eyes. If contact occurs, rinse eyes thoroughly with water.
- Do not inhale.

Stop use and ask a doctor

if irritation or redness develops and lasts.

Keep out of reach of children

In case of accidental ingestion, get medical help or contact Poison Control Center immediately.

Directions

- For occassional and Personal use.
- Rub thoroughly into hands for at least 30 seconds. Allo to dry.
- Children under 6 years should be supervised when using this product.

Other Information

Store between 15 - 30o C (59-86 oF).
Avoid Freezing and excessive heat above 40 oC (104oF)

Inactive Ingredients

Water (Aqua), PEG-6, AMP-Acrylates/vinyl Isodecanoate Crosspolymer, Fragrance (Parfum), Isopropyl Alcohol, Glycerin,Isopropyl Myristate, Tocopheryl Acetate, Aloe Barbadensis Leaf Juice., Yellow 5 (CI 19140 and BlUE 1 (CI 42090.

Questions

1-800-910-6874